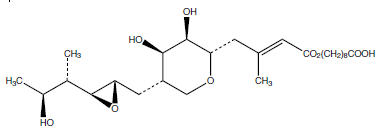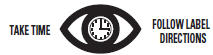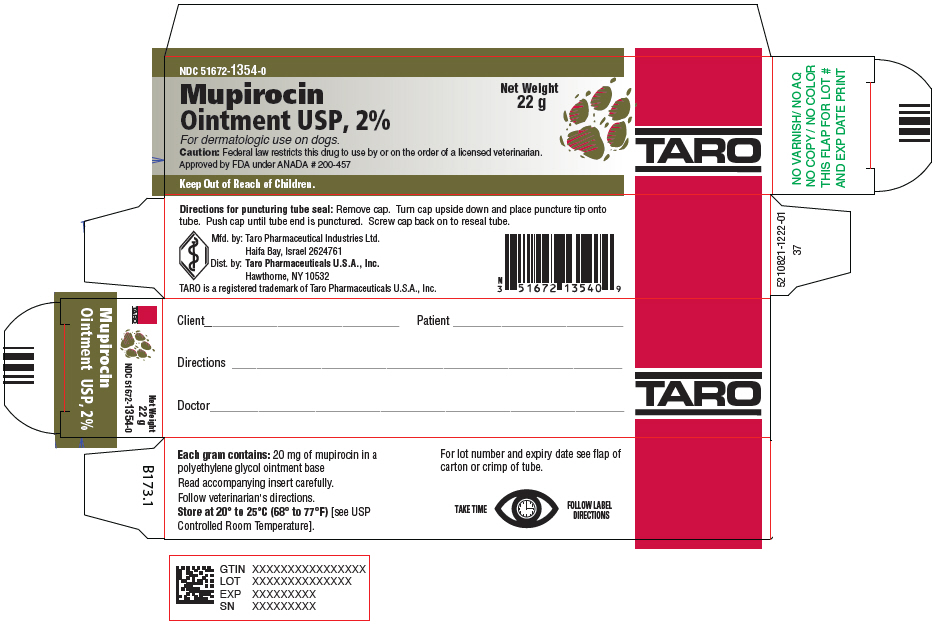 DRUG LABEL: Mupirocin
NDC: 51672-1354 | Form: OINTMENT
Manufacturer: Taro Pharmaceuticals U.S.A., Inc.
Category: animal | Type: PRESCRIPTION ANIMAL DRUG LABEL
Date: 20230927

ACTIVE INGREDIENTS: Mupirocin 20 mg/1 g
INACTIVE INGREDIENTS: polyethylene glycol 400; polyethylene glycol 3350

Mupirocin
Ointment USP, 2%

For dermatologic use on dogs

CAUTION

Federal law restricts this drug to use by or on the order of a licensed veterinarian.

DESCRIPTION

Each gram of mupirocin ointment contains 20 mg of mupirocin in a bland, water-washable ointment base consisting of polyethylene glycol 400 and polyethylene glycol 3350 (polyethylene glycol ointment). Mupirocin is a naturally-occurring, broad-spectrum antibiotic. The chemical name is 9-4-[5S-(2S,3S-epoxy-5S-hydroxy-4S-methylhexyl)-3R,4R-dihydroxytetrahydropyran-2S-yl]-3-methylbut-2(E)-enoyloxy-nonanoic acid. The chemical structure is:

CLINICAL PHARMACOLOGY

Mupirocin is a chemical entity produced by fermentation of the organism Pseudomonas fluorescens. Mupirocin inhibits bacterial protein synthesis by reversibly and specifically binding to bacterial isoleucyl transfer-RNA synthetase. Due to this mode of action, mupirocin shows no cross resistance with chloramphenicol, erythromycin, gentamicin, lincomycin, neomycin, novobiocin, penicillin, streptomycin, and tetracycline. Mupirocin is an antimicrobial agent that inhibits the growth of gram-positive and gram-negative bacteria.

Bacteria susceptible to the action of mupirocin in vitro include the aerobic isolates of Staphylococcus aureus (including methicillin-resistant strains and β-lactamase-producing strains), Staphylococcus intermedius, Staphylococcus epidermidis, other coagulase positive or negative Staphylococci, α-hemolytic Streptococci, β group A Streptococci (including S. pyogenes), other β Streptococci (including S. agalactiae), group D Streptococci (including S. faecalis and S. faecium), group Viridans Streptococci, Streptococcus pneumoniae, Corynebacterium hofmanii, Bacillus subtilis, Escherichia coli, Klebsiella pneumoniae, Proteus mirabilis, Proteus vulgaris, Enterobacter cloacae, Enterobacter aerogenes, Citrobacter freundii, Hemophilus influenzae (including β-lactamase-producing strains), Neisseria gonorrheae (including β-lactamase-producing strains), Neisseria meningitidis, Branhamella catarrhalis and Pasteurella multocida, and the anaerobic isolates of Peptostreptococcus anaerobius, Clostridium difficile, and Clostridium sporogenes.

Clinical significance of the in vitro data is unknown except for susceptible strains of Staphylcoccus aureus and Staphylococcus intermedius.

INDICATIONS FOR USE

Mupirocin ointment is indicated for the topical treatment of canine bacterial infections of the skin, including superficial pyoderma, caused by susceptible strains of Staphylococcus aureus and Staphylococcus intermedius.

CONTRAINDICATIONS

This drug is contraindicated in animals with a history of sensitivity reactions to any of its components.

WARNINGS

Because of the potential hazard of nephrotoxicity due to the polyethylene glycol content of the base, care should be exercised when using this product in treating extensive deep lesions where absorption of large quantities of polyethylene glycol is possible.

Safety of use in pregnant or breeding animals has not been determined.

Mupirocin ointment is not for ophthalmic use.

ADVERSE REACTIONS

No adverse reactions have been reported with this product. If a skin reaction such as irritation should occur, treatment should be discontinued and appropriate therapy instituted.

DOSAGE AND ADMINISTRATION

Prior to treatment, the lesion should be cleansed. Mupirocin ointment should be applied to the affected area twice a day. Apply a sufficient amount of ointment to completely cover the infected area. Maximum duration of treatment should not exceed 30 days.

HOW SUPPLIED

Mupirocin ointment is supplied in 5 g, 15 g, 22 g, and 30 g tubes.

STORAGE AND HANDLING

Store at 20° to 25°C (68° to 77°F) [see USP Controlled Room Temperature]

Keep Out of Reach of Children

Approved by FDA under ANADA # 200-457

Mfd. by: Taro Pharmaceutical Industries Ltd.
Haifa Bay, Israel 2624761

Dist. by: Taro Pharmaceuticals U.S.A., Inc.
Hawthorne, NY 10532

Revised: November 2020

5210551-1120-0 37

PRINCIPAL DISPLAY PANEL - 22 g Tube Carton

NDC 51672-1354-0

Mupirocin
Ointment USP, 2%

For dermatologic use on dogs.
Caution: Federal law restricts this drug to use by or on the order of a licensed veterinarian.
Approved by FDA under ANADA # 200-457

Net Weight
22 g

Keep Out of Reach of Children.

TARO